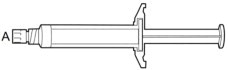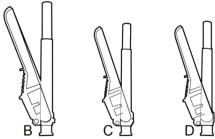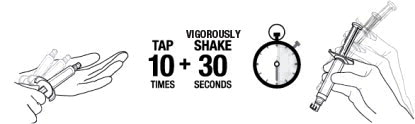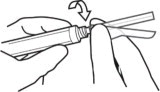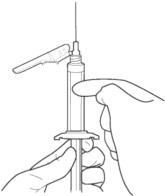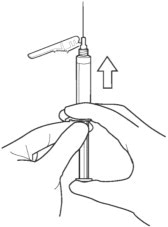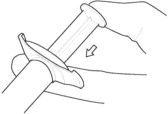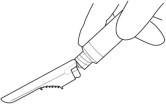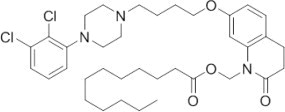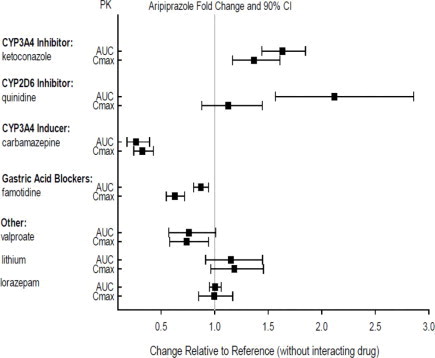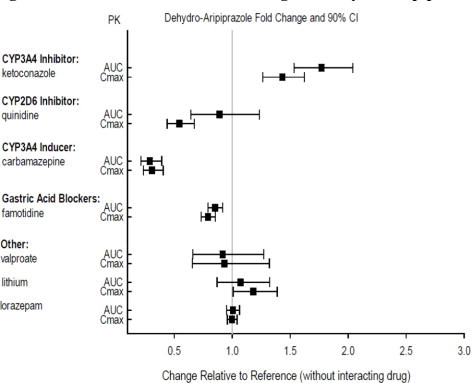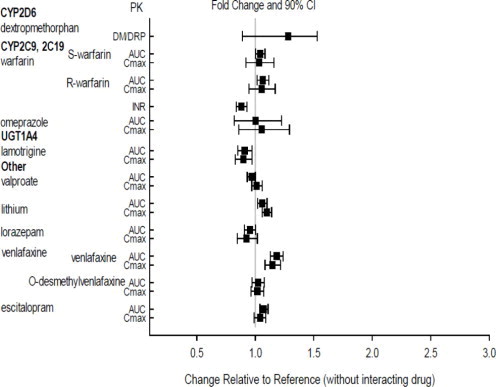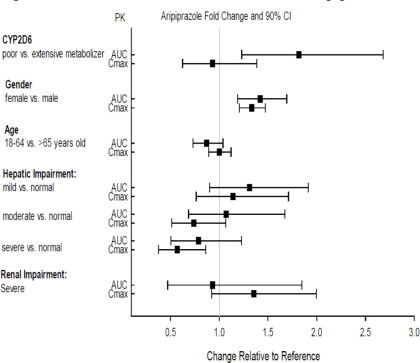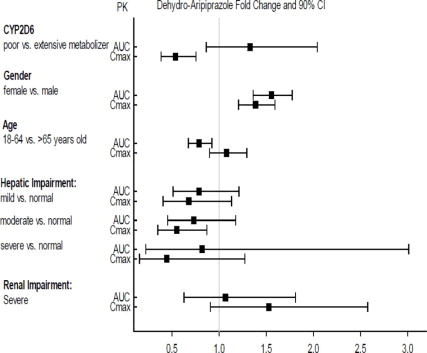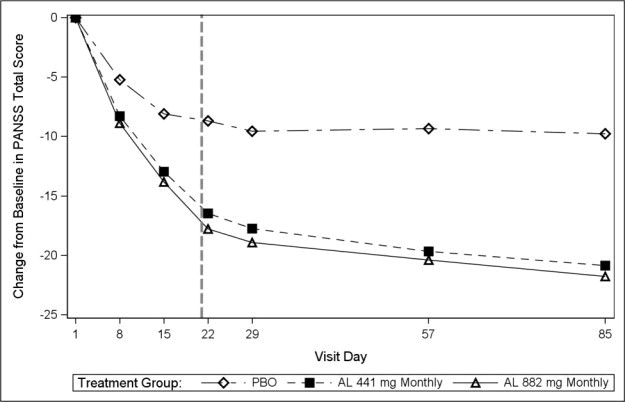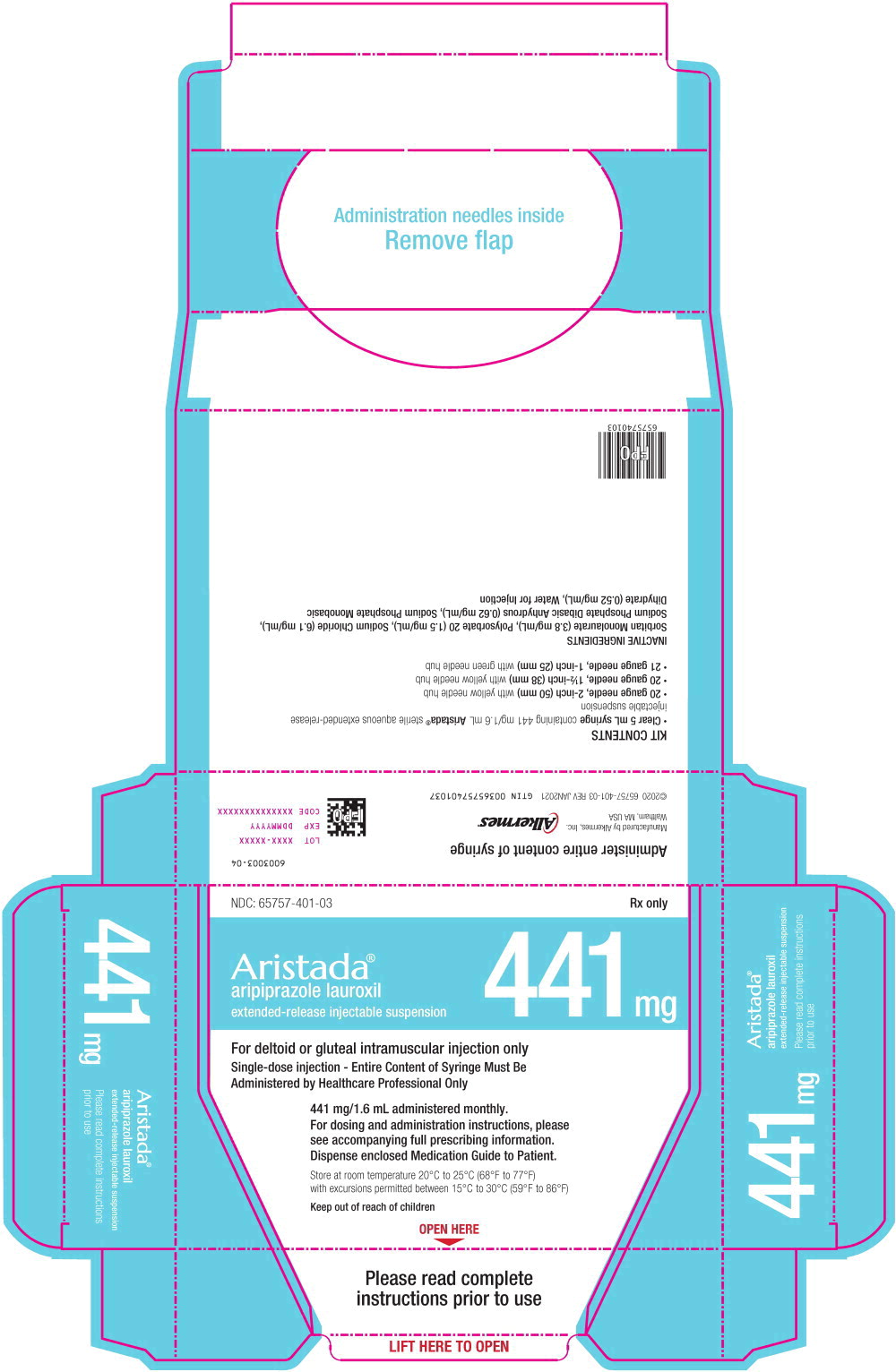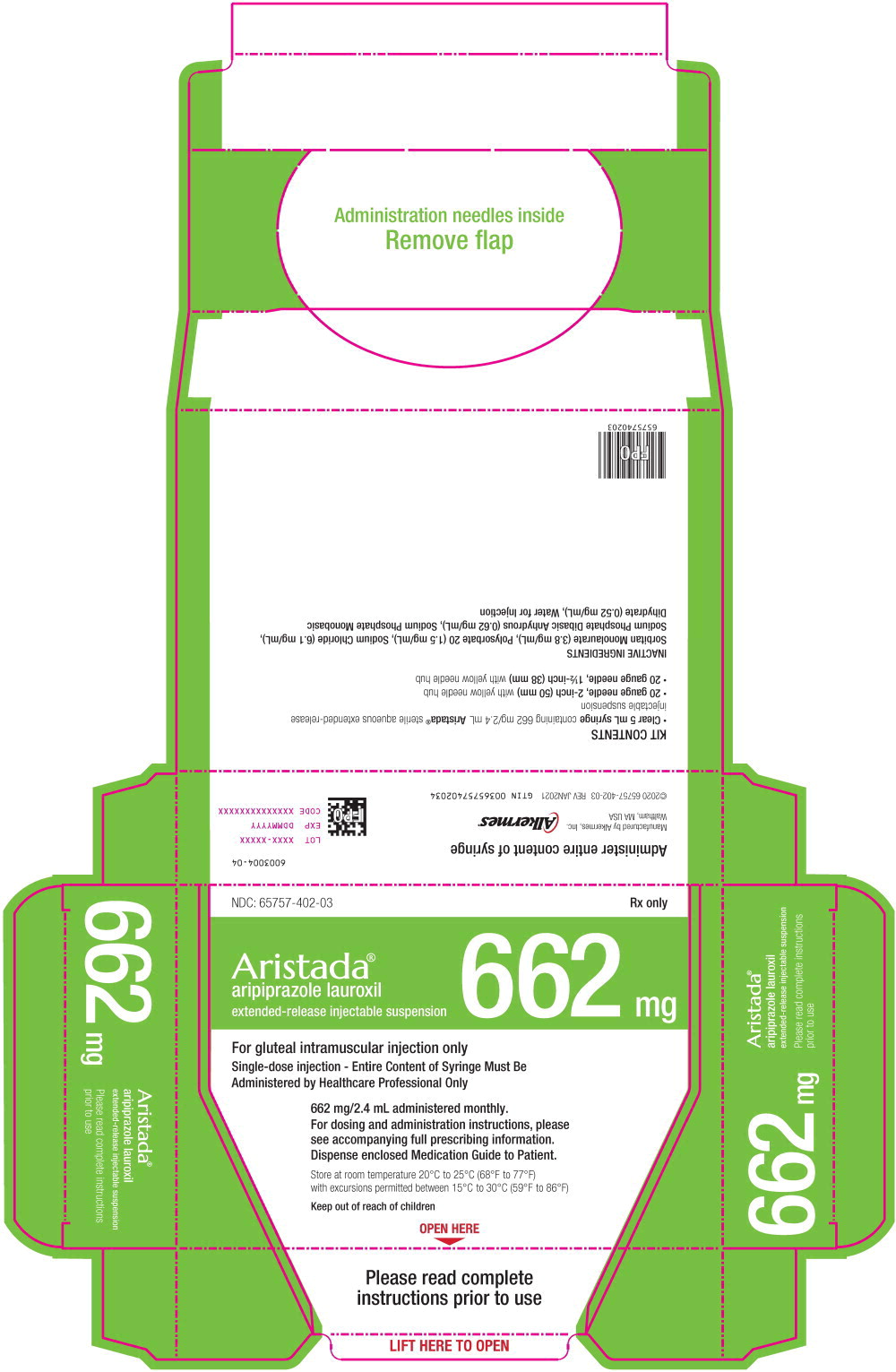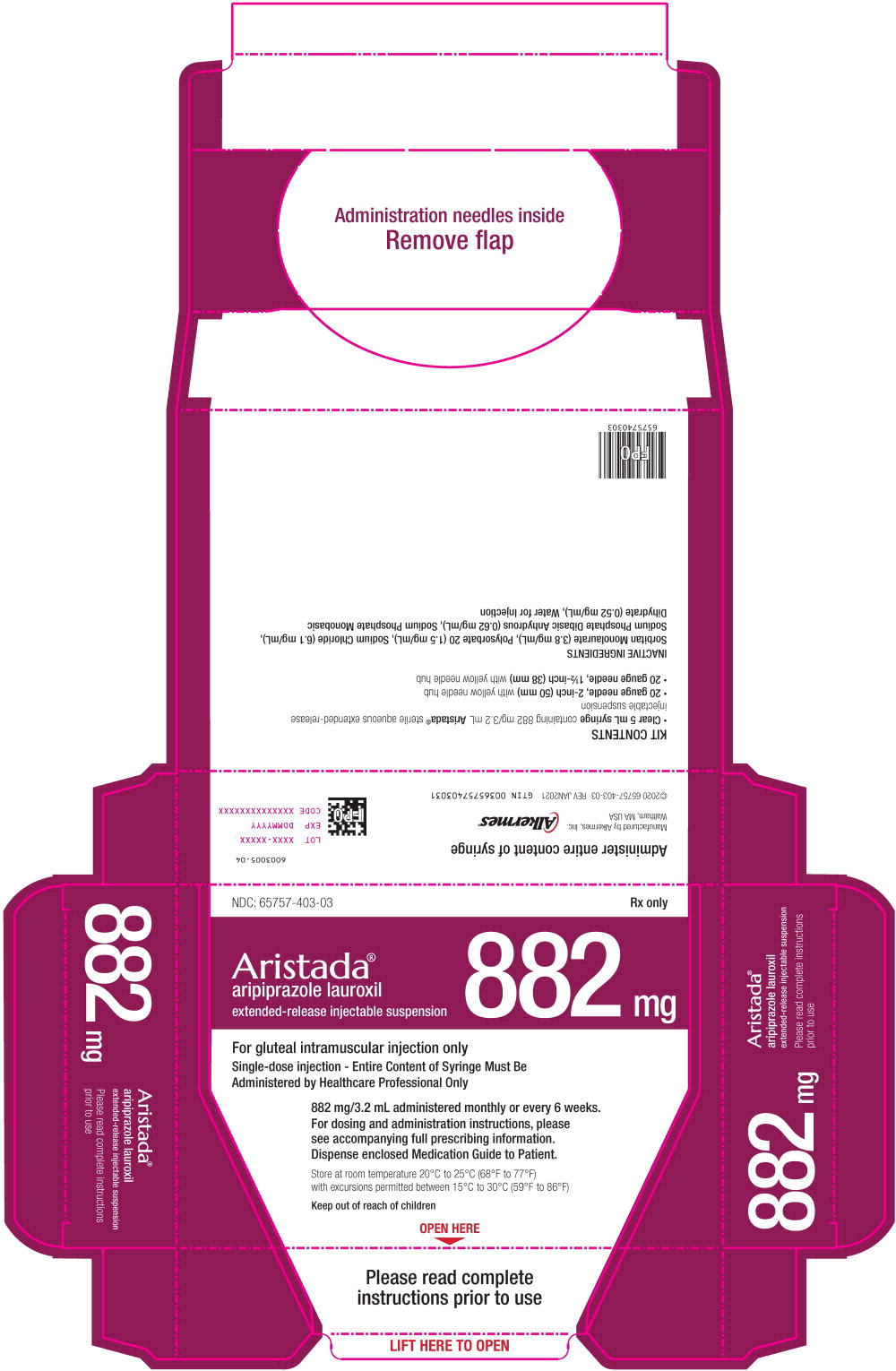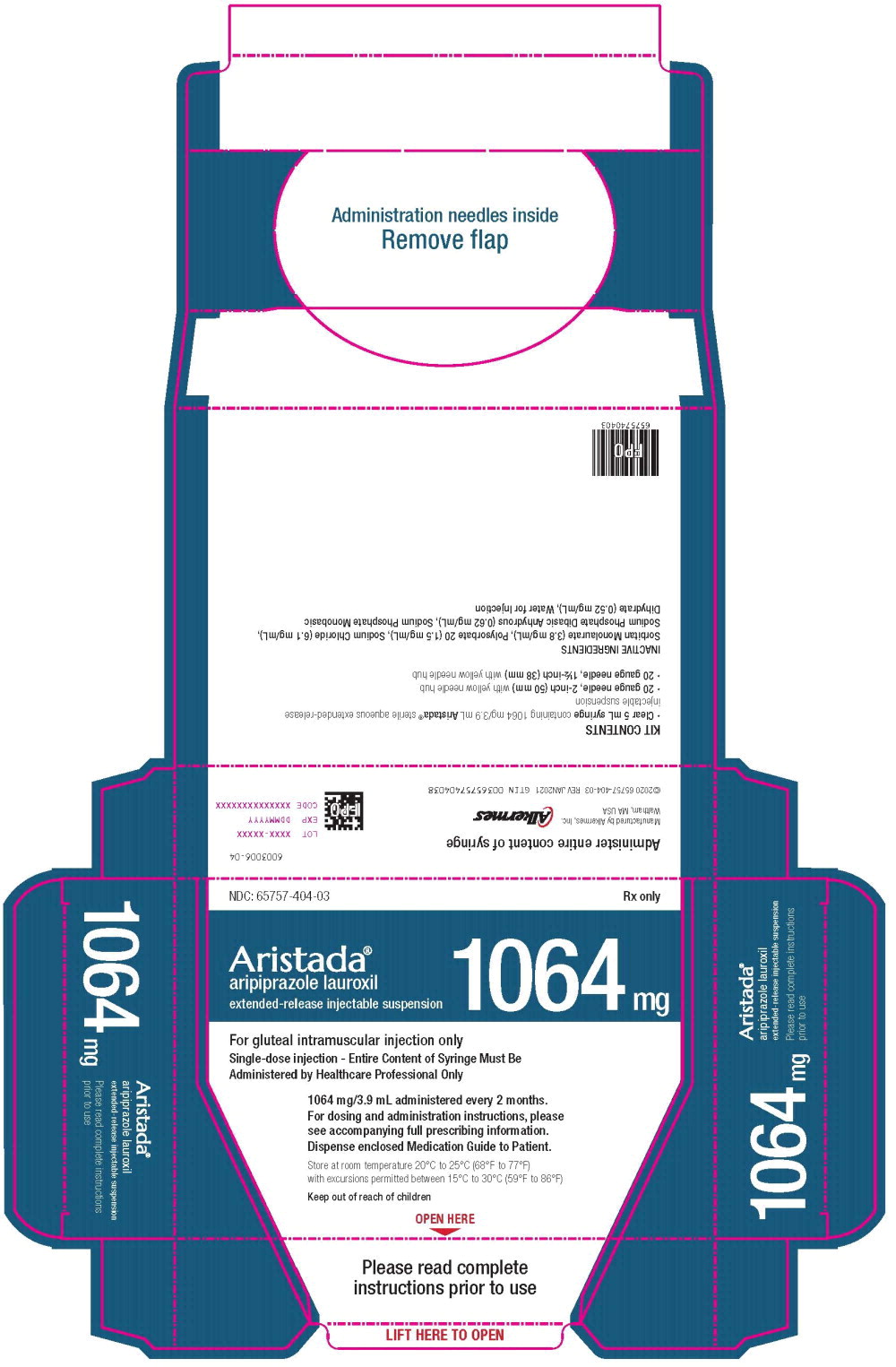 DRUG LABEL: ARISTADA
NDC: 65757-401 | Form: INJECTION, SUSPENSION, EXTENDED RELEASE
Manufacturer: Alkermes, Inc.
Category: prescription | Type: HUMAN PRESCRIPTION DRUG LABEL
Date: 20250128

ACTIVE INGREDIENTS: aripiprazole lauroxil 441 mg/1.6 mL
INACTIVE INGREDIENTS: Sorbitan Monolaurate; Polysorbate 20; Sodium Chloride; Sodium Phosphate, Dibasic, Anhydrous; Sodium Phosphate, Monobasic, Dihydrate; Water

HIGHLIGHTS OF PRESCRIBING INFORMATION

These highlights do not include all the information needed to use ARISTADA® safely and effectively. See full prescribing information for ARISTADA®.
ARISTADA® (aripiprazole lauroxil) extended-release injectable suspension, for intramuscular use
Initial U.S. Approval: 2015

WARNING: INCREASED MORTALITY IN ELDERLY PATIENTS WITH DEMENTIA-RELATED PSYCHOSIS

See full prescribing information for complete boxed warning.

- Elderly patients with dementia-related psychosis treated with antipsychotic drugs are at an increased risk of death. (5.1)
- ARISTADA is not approved for the treatment of patients with dementia-related psychosis. (5.1)

1 INDICATIONS AND USAGE

ARISTADA is an atypical antipsychotic indicated for the treatment of schizophrenia in adults (1).

2 DOSAGE AND ADMINISTRATION

- Administer ARISTADA by intramuscular injection in the deltoid (441 mg dose only) or gluteal (441 mg, 662 mg, 882 mg or 1064 mg) muscle by a healthcare professional (2.1).
- For patients naïve to aripiprazole, establish tolerability with oral aripiprazole prior to initiating treatment with ARISTADA (2.1).
- There are two options for initiating treatment with ARISTADA:
  - Option #1: Administer one injection of 675 mg of ARISTADA INITIO® and one 30 mg dose of oral aripiprazole in conjunction with the first ARISTADA injection. (2.1).
  - Option #2: Administer 21 consecutive days of oral aripiprazole in conjunction with the first ARISTADA injection (2.1).
- ARISTADA can be initiated at a dose of 441 mg, 662 mg or 882 mg administered monthly, 882 mg dose every 6 weeks, or 1064 mg dose every 2 months (2.1).
- Dosing regimen adjustments may be required for missed doses (2.2).
- Dose adjustments are required for 1) known CYP2D6 poor metabolizers and 2) for patients taking CYP3A4 inhibitors, CYP2D6 inhibitors, or CYP3A4 inducers for more than 2 weeks (2.4).

3 DOSAGE FORMS AND STRENGTHS

Extended-release injectable suspension: 441 mg, 662 mg, 882 mg or 1064 mg single-dose pre-filled syringe (3)

4 CONTRAINDICATIONS

Known hypersensitivity to aripiprazole (4)

5 WARNINGS AND PRECAUTIONS

- Cerebrovascular Adverse Reactions in Elderly Patients with Dementia-Related Psychosis: Increased incidence of cerebrovascular adverse reactions (e.g., stroke, transient ischemia attack, including fatalities) (5.2).
- Potential for Dosing and Medication Errors: Substitution and dispensing errors between ARISTADA and ARISTADA INITIO could occur. Do not substitute ARISTADA INITIO for ARISTADA (5.3).
- Neuroleptic Malignant Syndrome: Manage with immediate discontinuation and close monitoring (5.4).
- Tardive Dyskinesia: Discontinue if clinically appropriate (5.5).
- Metabolic Changes: Monitor for hyperglycemia, dyslipidemia, and weight gain (5.6).
- Pathological Gambling and Other Compulsive Behaviors: Consider dose reduction or discontinuation (5.7).
- Orthostatic Hypotension: Monitor heart rate and blood pressure and warn patients with known cardiovascular or cerebrovascular disease, and risk of dehydration or syncope (5.8).
- Leukopenia, Neutropenia, and Agranulocytosis: Perform complete blood counts in patients with a history of a clinically significant low white blood cell (WBC) count. Consider discontinuation if clinically significant decline in WBC in the absence of other causative factors (5.10).
- Seizures: Use cautiously in patients with a history of seizures or with conditions that lower the seizure threshold (5.11).
- Potential for Cognitive and Motor Impairment: Use caution when operating machinery (5.12).

6 ADVERSE REACTIONS

Most commonly observed adverse reaction with ARISTADA (incidence ≥5% and at least twice that for placebo) was akathisia (6.1).

To report SUSPECTED ADVERSE REACTIONS, contact Alkermes, Inc. at 1-866-274-7823 or FDA at 1-800-FDA-1088 or www.fda.gov/medwatch.

8 USE IN SPECIFIC POPULATIONS

- Pregnancy: May cause extrapyramidal and/or withdrawal symptoms in neonates in women exposed during the third trimester of pregnancy (8.1).
- Lactation: Monitor the breastfed infant for dehydration and lack of appropriate weight gain (8.2).

FULL PRESCRIBING INFORMATION

WARNING: INCREASED MORTALITY IN ELDERLY PATIENTS WITH DEMENTIA-RELATED PSYCHOSIS

Elderly patients with dementia-related psychosis treated with antipsychotic drugs are at an increased risk of death. ARISTADA is not approved for the treatment of patients with dementia-related psychosis [see Warnings and Precautions (5.1)].

1 INDICATIONS AND USAGE

ARISTADA is indicated for the treatment of schizophrenia in adults [see Clinical Studies (14)].

2 DOSAGE AND ADMINISTRATION

2.1 Recommended Dosage

ARISTADA is only to be administered as an intramuscular injection by a healthcare professional. For patients who have never taken aripiprazole, establish tolerability with oral aripiprazole prior to initiating treatment with ARISTADA. Due to the half-life of oral aripiprazole, it may take up to 2 weeks to fully assess tolerability. Refer to the prescribing information of oral aripiprazole for the recommended dosage and administration of the oral formulation.

There are two ways to initiate treatment with ARISTADA:

- Option #1: Administer one intramuscular injection of ARISTADA INITIO 675 mg (in either the deltoid or gluteal muscle) and one dose of oral aripiprazole 30 mg in conjunction with the first ARISTADA injection.
  - The first ARISTADA injection may be administered on the same day as ARISTADA INITIO or up to 10 days thereafter. See the ARISTADA INITIO prescribing information for additional information regarding administration of ARISTADA INITIO.
  - Avoid injecting both ARISTADA INITIO and ARISTADA concomitantly into the same deltoid or gluteal muscle.
- Option #2: Administer 21 consecutive days of oral aripiprazole in conjunction with the first ARISTADA injection.

Depending on individual patient's needs, treatment with ARISTADA can be initiated at a dose of 441 mg, 662 mg or 882 mg administered monthly, 882 mg administered every 6 weeks or 1064 mg administered every 2 months. The 441 mg, 662 mg, 882 mg and 1064 mg doses correspond to 300 mg, 450 mg, 600 mg and 724 mg of aripiprazole, respectively [see Clinical Pharmacology (12.3)].

Table 1: ARISTADA Dosing Frequency and Site of Injection
Dose | Dosing Frequency | Site of Intramuscular Injection
441 mg | Monthly | Deltoid or Gluteal
662 mg | Monthly | Gluteal
882 mg | Monthly or every 6 weeks | Gluteal
1064 mg | Every 2 months | Gluteal

Use the following ARISTADA doses for patients who are stabilized on oral aripiprazole, as shown in Table 2.

Table 2: ARISTADA Doses Based on Oral Aripiprazole Total Daily Dose
Oral Aripiprazole Dose | Intramuscular ARISTADA Dose
10 mg per day | 441 mg every month
15 mg per day | 662 mg every month 882 mg every 6 weeks 1064 mg every 2 months
20 mg or higher per day | 882 mg every month

In conjunction with the first ARISTADA injection, administer a single injection of ARISTADA INITIO and one dose of oral aripiprazole 30 mg, or continue treatment with oral aripiprazole for 21 consecutive days [see Recommended Dosage (2.1)].

Adjust the ARISTADA dose as needed. When making dose and dosing interval adjustments, consider the pharmacokinetics and prolonged-release characteristics of ARISTADA [see Clinical Pharmacology (12.3)].

2.2 Missed Doses

When a dose of ARISTADA is missed, administer the next injection of ARISTADA as soon as possible. Depending on the time elapsed since the last ARISTADA injection, supplement the next ARISTADA injection as recommended in Table 3 below.

Table 3: Recommendation for Concomitant Supplementation Following Missed Doses of ARISTADA
Dose of Patient's Last ARISTADA Injection | Length of Time Since Last Injection
441 mg | ≤ 6 weeks | > 6 and ≤ 7 weeks | > 7 weeks
662 mg | ≤ 8 weeks | > 8 and ≤ 12 weeks | > 12 weeks
882 mg | ≤ 8 weeks | > 8 and ≤ 12 weeks | > 12 weeks
1064 mg | ≤ 10 weeks | > 10 and ≤ 12 weeks | > 12 weeks
Dosage and Administration for Re-initiation of ARISTADA | No Supplementation Required | Supplement with a Single Dose of ARISTADA INITIO OR 7 Days of Oral Aripiprazolea | Re-initiate with a Single Dose of ARISTADA INITIO and a Single Dose of Oral Aripiprazole 30 mg OR supplement with 21 Days of Oral Aripiprazolea
a The patient should supplement with the same dose of oral aripiprazole as when the patient began ARISTADA (see Table 2).

2.3 Early Dosing

The recommended ARISTADA dosing interval is monthly for the 441 mg, 662 mg and 882 mg doses, every 6 weeks for the 882 mg dose, or every 2 months for the 1064 mg dose and should be maintained. In the event of early dosing, an ARISTADA injection should not be given earlier than 14 days after the previous injection.

2.4 Dose Adjustments for CYP450 Considerations

Refer to the prescribing information for oral aripiprazole for recommendations regarding dosage adjustments due to drug interactions, for the first 21 days when the patient is taking 21 days of oral aripiprazole concomitantly with the first dose of ARISTADA. Avoid initiating ARISTADA treatment with ARISTADA INITIO in patients requiring dose adjustments.

Once stabilized on ARISTADA, refer to the dosing recommendations below for patients taking strong CYP2D6 inhibitors, strong CYP3A4 inhibitors, or strong CYP3A4 inducers:

- No dosage changes recommended for ARISTADA, if CYP450 modulators are added for less than 2 weeks.
- Make dose changes to ARISTADA if CYP450 modulators are added for greater than 2 weeks (see Table 4).

Table 4: ARISTADA Dose Adjustments with Concomitant CYP450 Modulator Use
Concomitant Medicine | Dose Change for ARISTADAa
Strong CYP3A4 Inhibitor | Reduce the dose of ARISTADA to the next lower strength. No dosage adjustment is necessary in patients taking 441 mg ARISTADA, if tolerated. For patients known to be poor metabolizers of CYP2D6: Reduce dose to 441 mg from 662 mg, 882 mg, or 1064 mg. No dosage adjustment is necessary in patients taking 441 mg ARISTADA, if tolerated.
Strong CYP2D6 Inhibitor | Reduce the dose of ARISTADA to the next lower strength. No dosage adjustment is necessary in patients taking 441 mg ARISTADA, if tolerated. For patients known to be poor metabolizers of CYP2D6: No dose adjustment required.
Both Strong CYP3A4 Inhibitor and Strong CYP2D6 Inhibitor | Avoid use for patients at 662 mg, 882 mg, or 1064 mg dose. No dosage adjustment is necessary in patients taking 441 mg ARISTADA, if tolerated.
CYP3A4 Inducers | No dose adjustment for 662 mg, 882 mg, or 1064 mg dose; increase the 441 mg dose to 662 mg.
a For the 882 mg dose administered every 6 weeks and the 1064 mg administered every 2 months, the next lower strength should be 441 mg administered monthly.

2.5 Important Administration Instructions

The kit contains a syringe containing ARISTADA sterile aqueous extended-release injectable suspension and 2 or 3 safety needles depending on dose (a 2-inch 20 gauge needle with yellow needle hub, a 1 ½-inch 20 gauge needle with yellow needle hub, and a 1-inch 21 gauge needle with green needle hub (441 mg kit only)) for intramuscular injection. All materials should be stored at room temperature.

A | 5 mL syringe containing ARISTADA sterile aqueous extended-release injectable suspension

B | 20 gauge needle, 2-inch with yellow needle hub

C | 20 gauge needle, 1½-inch with yellow needle hub

D | 21 gauge needle, 1-inch with green needle hub

1. TAP and vigorously SHAKE the syringe.

1a. Tap the syringe at least 10 times to dislodge any material which may have settled.

1b. Shake the syringe vigorously for a minimum of 30 seconds to ensure a uniform suspension. If the syringe is not used within 15 minutes, shake again for 30 seconds.

2. SELECT the injection needle.

2a. Select injection site.

2b. Select needle length based on injection site. For patients with a larger amount of subcutaneous tissue overlaying the injection site muscle, use the longer of the needles provided.

Table 5: Injection Site and Associated Needle Length
Injection Site | Needle Length
441 mg dose
Deltoid | 21 gauge, 1-inch or 20 gauge, 1½-inch
Gluteal | 20 gauge, 1½-inch or 20 gauge, 2-inch
662 mg dose
Gluteal | 20 gauge, 1½-inch or 20 gauge, 2-inch
882 mg dose
Gluteal | 20 gauge, 1½-inch or 20 gauge, 2-inch
1064 mg dose
Gluteal | 20 gauge, 1½-inch or 20 gauge, 2-inch

[see Dosage and Administration (2.1)]

3. ATTACH the injection needle.

Attach the appropriate needle securely with a clockwise twisting motion. Do NOT overtighten. Overtightening could lead to needle hub cracking.

4. PRIME the syringe to remove air.

4a. Bring the syringe into upright position and tap the syringe to bring air to the top.

4b. Depress the plunger rod to remove air until a few drops are released. It is normal to see small air bubbles remaining in the syringe.

5. Inject in a RAPID and CONTINUOUS manner. Product requires a RAPID injection. Do not hesitate. Administer the entire content intramuscularly. Do not inject by any other route.

6. DISPOSE of the needle. Cover the needle by pressing the safety device. Dispose of used and unused items in a proper waste container.

3 DOSAGE FORMS AND STRENGTHS

ARISTADA is a white to off-white aqueous extended-release injectable suspension provided in a single-dose pre-filled syringe.

ARISTADA is available as described in Table 6.

Table 6: Presentations of ARISTADA
Dose Strength | Volume | Inject Intramuscularly | Color Label
441 mg | 1.6 mL | Deltoid or Gluteal Muscle | Light Blue
662 mg | 2.4 mL | Gluteal Muscle Only | Green
882 mg | 3.2 mL | Gluteal Muscle Only | Burgundy
1064 mg | 3.9 mL | Gluteal Muscle Only | Dark Blue

4 CONTRAINDICATIONS

ARISTADA is contraindicated in patients with a known hypersensitivity reaction to aripiprazole. Hypersensitivity reactions have ranged from pruritus/urticaria to anaphylaxis [see Adverse Reactions (6)].

5 WARNINGS AND PRECAUTIONS

5.1 Increased Mortality in Elderly Patients with Dementia-related Psychosis

Elderly patients with dementia-related psychosis treated with antipsychotic drugs are at an increased risk of death. Analyses of 17 placebo-controlled trials (modal duration of 10 weeks), largely in patients taking atypical antipsychotic drugs, revealed a risk of death in drug-treated patients of between 1.6 to 1.7 times the risk of death in placebo-treated patients. Over the course of a typical 10-week controlled trial, the rate of death in drug-treated patients was about 4.5%, compared to a rate of about 2.6% in the placebo group.

Although the causes of death were varied, most of the deaths appeared to be either cardiovascular (e.g., heart failure, sudden death) or infectious (e.g., pneumonia) in nature. Observational studies suggest that, similar to atypical antipsychotic drugs, treatment with conventional antipsychotic drugs may increase mortality. The extent to which the findings of increased mortality in observational studies may be attributed to the antipsychotic drug as opposed to some characteristic(s) of the patients is not clear. ARISTADA is not approved for the treatment of patients with dementia-related psychosis [see Boxed Warning, Warnings and Precautions (5.2)].

5.2 Cerebrovascular Adverse Reactions, Including Stroke

In placebo-controlled trials with risperidone, aripiprazole, and olanzapine in elderly patients with dementia, there was a higher incidence of cerebrovascular adverse reactions (cerebrovascular accidents and transient ischemic attacks) including fatalities compared to placebo-treated patients. ARISTADA is not approved for the treatment of patients with dementia-related psychosis [see Boxed Warning, Warnings and Precautions (5.1)].

5.3 Potential for Dosing and Medication Errors

Medication errors, including substitution and dispensing errors, between ARISTADA and ARISTADA INITIO could occur. ARISTADA INITIO is for single administration in contrast to ARISTADA which is administered monthly, every 6 weeks, or every 8 weeks [see Dosage and Administration (2.1)]. Do not substitute ARISTADA INITIO for ARISTADA because of differing pharmacokinetic profiles [see Clinical Pharmacology (12.3)].

5.4 Neuroleptic Malignant Syndrome

A potentially fatal symptom complex sometimes referred to as Neuroleptic Malignant Syndrome (NMS) may occur in association with antipsychotic drugs, including ARISTADA. Clinical manifestations of NMS are hyperpyrexia, muscle rigidity, altered mental status, and evidence of autonomic instability (irregular pulse or blood pressure, tachycardia, diaphoresis, and cardiac dysrhythmia). Additional signs may include elevated creatine phosphokinase, myoglobinuria (rhabdomyolysis), and acute renal failure.

The diagnostic evaluation of patients with this syndrome is complicated. In arriving at a diagnosis, it is important to identify cases in which the clinical presentation includes both serious medical illness (e.g., pneumonia, systemic infection, etc.) and untreated or inadequately treated extrapyramidal signs and symptoms (EPS). Other important considerations in the differential diagnosis include central anticholinergic toxicity, heat stroke, drug fever, and primary central nervous system pathology.

The management of NMS should include: (1) immediate discontinuation of antipsychotic drugs and other drugs not essential to concurrent therapy; (2) intensive symptomatic treatment and medical monitoring; and (3) treatment of any concomitant serious medical problems for which specific treatments are available. There is no general agreement about specific pharmacological treatment regimens for uncomplicated NMS.

If a patient appears to require antipsychotic drug treatment after recovery from NMS, reintroduction of drug therapy should be closely monitored, since recurrences of NMS have been reported.

5.5 Tardive Dyskinesia

A syndrome of potentially irreversible, involuntary, dyskinetic movements may develop in patients treated with antipsychotic drugs. Although the prevalence of the syndrome appears to be highest among the elderly, especially elderly women, it is impossible to predict which patients will develop the syndrome. Whether antipsychotic drug products differ in their potential to cause tardive dyskinesia is unknown.

The risk of developing tardive dyskinesia and the likelihood that it will become irreversible appear to increase as the duration of treatment and the total cumulative dose of antipsychotic drugs administered to the patient increase, but the syndrome can develop after relatively brief treatment periods at low doses, although this is uncommon.

Tardive dyskinesia may remit, partially or completely, if antipsychotic treatment is withdrawn. Antipsychotic treatment itself may suppress (or partially suppress) the signs and symptoms of the syndrome and may thus mask the underlying process. The effect of symptomatic suppression on the long-term course of the syndrome is unknown.

Given these considerations, ARISTADA should be prescribed in a manner that is most likely to minimize the occurrence of tardive dyskinesia. Chronic antipsychotic treatment should generally be reserved for patients who suffer from a chronic illness that is known to respond to antipsychotic drugs. In patients who do require chronic treatment, the smallest dose and the shortest duration of treatment producing a satisfactory clinical response should be sought. The need for continued treatment should be reassessed periodically.

If signs and symptoms of tardive dyskinesia appear in a patient treated with ARISTADA drug discontinuation should be considered. However, some patients may require treatment with ARISTADA despite the presence of the syndrome.

5.6 Metabolic Changes

Atypical antipsychotic drugs have been associated with metabolic changes that include hyperglycemia/diabetes mellitus, dyslipidemia, and weight gain. While all drugs in the class have been shown to produce some metabolic changes, each drug has its own specific risk profile.

Hyperglycemia/ Diabetes Mellitus

Hyperglycemia, in some cases extreme and associated with ketoacidosis or hyperosmolar coma or death, has been reported in patients treated with atypical antipsychotics. There have been reports of hyperglycemia in patients treated with oral aripiprazole. Assessment of the relationship between atypical antipsychotic use and glucose abnormalities is complicated by the possibility of an increased background risk of diabetes mellitus in patients with schizophrenia and the increasing incidence of diabetes mellitus in the general population. Given these confounders, the relationship between atypical antipsychotic use and hyperglycemia-related adverse events is not completely understood. However, epidemiological studies suggest an increased risk of hyperglycemia-related adverse reactions in patients treated with the atypical antipsychotics.

Patients with an established diagnosis of diabetes mellitus who are started on atypical antipsychotics should be monitored regularly for worsening of glucose control. Patients with risk factors for diabetes mellitus (e.g., obesity, family history of diabetes) who are starting treatment with atypical antipsychotics should undergo fasting blood glucose testing at the beginning of treatment and periodically during treatment. Any patient treated with atypical antipsychotics should be monitored for symptoms of hyperglycemia including polydipsia, polyuria, polyphagia, and weakness. Patients who develop symptoms of hyperglycemia during treatment with atypical antipsychotics should undergo fasting blood glucose testing. In some cases, hyperglycemia has resolved when the atypical antipsychotic was discontinued; however, some patients require continuation of anti-diabetic treatment despite discontinuation of the suspect drug.

In the long-term, open-label schizophrenia study with ARISTADA, 14% of patients with normal hemoglobin A1c (<5.7%) at baseline developed elevated levels (≥5.7%) post-baseline.

Dyslipidemia

Undesirable alterations in lipids have been observed in patients treated with atypical antipsychotics.

In the long-term, open-label schizophrenia study with ARISTADA, shifts in baseline fasting total cholesterol from normal (<200 mg/dL) to high (≥240 mg/dL) were reported in 1% of patients; shifts in baseline fasting LDL cholesterol from normal (<100 mg/dL) to high (≥160 mg/dL) were reported in 1% of patients; and shifts in baseline fasting triglycerides from normal (<150 mg/dL) to high (≥200 mg/dL) were reported in 8% of patients. In the same study, shifts in baseline fasting total cholesterol from borderline (≥ 200 mg/dL and <240 mg/dL) to high (≥240 mg/dL) were reported in 15% of patients; shifts in baseline fasting LDL cholesterol from borderline (≥100 mg/dL and <160 mg/dL) to high (≥160 mg/dL) were reported in 8% of patients; and shifts in baseline fasting triglycerides from borderline (≥150 mg/dL and <200 mg/dL) to high (≥200 mg/dL) were reported in 35% of patients. In addition, the proportion of patients with shifts in fasting HDL cholesterol from normal (≥40 mg/dL) to low (<40 mg/dL) was reported in 15% of patients.

Weight Gain

Weight gain has been observed with atypical antipsychotic use. Clinical monitoring of weight is recommended.

The proportion of adult patients with weight gain ≥7% of body weight is presented in Table 7.

Table 7: Proportion of Adult Patients with Shifts in Weight in the 12-Week, Placebo-Controlled, Fixed-Dose Schizophrenia Trial
 | Placebo N = 207 (%) | ARISTADA
 | Placebo N = 207 (%) | 441 mg N = 207 (%) | 882 mg N = 208 (%)
Weight Gain
≥7% increase from baseline | 6 | 10 | 9

5.7 Pathological Gambling and Other Compulsive Behaviors

Post-marketing case reports suggest that patients can experience intense urges, particularly for gambling, and the inability to control these urges while taking aripiprazole. Other compulsive urges, reported less frequently include: sexual urges, shopping, eating or binge eating, and other impulsive or compulsive behaviors. Because patients may not recognize these behaviors as abnormal, it is important for prescribers to ask patients or their caregivers specifically about the development of new or intense gambling urges, compulsive sexual urges, compulsive shopping, binge or compulsive eating, or other urges while being treated with aripiprazole. It should be noted that impulse-control symptoms can be associated with the underlying disorder. In some cases, although not all, urges were reported to have stopped when the dose was reduced or the medication was discontinued. Compulsive behaviors may result in harm for the patient and others if not recognized. Consider dose reduction or stopping the medication if a patient develops such urges.

5.8 Orthostatic Hypotension

Aripiprazole may cause orthostatic hypotension, perhaps due to its α1-adrenergic receptor antagonism. Associated adverse reactions related to orthostatic hypotension can include dizziness, lightheadedness and tachycardia. Generally, these risks are greatest at the beginning of treatment and during dose escalation. Patients at increased risk of these adverse reactions or at increased risk of developing complications from hypotension include those with dehydration, hypovolemia, treatment with antihypertensive medication, history of cardiovascular disease (e.g., heart failure, myocardial infarction, ischemia, or conduction abnormalities), history of cerebrovascular disease, as well as patients who are antipsychotic-naïve. In such patients, consider using a lower starting dose, and monitor orthostatic vital signs.

Orthostatic hypotension was reported for one patient in the ARISTADA 882 mg group (0.5%) and no patients in the ARISTADA 441 mg and placebo groups in the 12-week schizophrenia efficacy study [see Clinical Studies (14)]. In the long-term open-label schizophrenia study, orthostatic hypotension was reported for 1 (0.2%) patient treated with ARISTADA. Orthostatic hypotension was defined as a decrease in systolic blood pressure ≥20 mmHg accompanied by an increase in heart rate ≥25 bpm when comparing standing to supine values.

5.9 Falls

Antipsychotics including ARISTADA may cause somnolence, postural hypotension, or motor and sensory instability, which may lead to falls and, consequently, fractures or other injuries. For patients with diseases, conditions, or medications that could exacerbate these effects, complete fall risk assessments when initiating antipsychotic treatment and recurrently for those patients on long-term antipsychotic therapy.

5.10 Leukopenia, Neutropenia, and Agranulocytosis

In clinical trials and/or postmarketing experience, events of leukopenia and neutropenia have been reported temporally related to antipsychotic agents. Agranulocytosis has also been reported.

Possible risk factors for leukopenia/neutropenia include pre-existing low white blood cell count (WBC)/absolute neutrophil count (ANC) and history of drug-induced leukopenia/neutropenia. In patients with a history of a clinically significant low WBC/ANC or drug-induced leukopenia/neutropenia, perform a complete blood count (CBC) frequently during the first few months of therapy. In such patients, consider discontinuation of ARISTADA at the first sign of a clinical significant decline in WBC in the absence of other causative factors.

Monitor patients with clinically significant neutropenia for fever or other symptoms or signs of infection and treat promptly if such symptoms or signs occur. Discontinue ARISTADA in patients with severe neutropenia (absolute neutrophil count <1000/mm^3) and follow their WBC until recovery.

5.11 Seizures

As with other antipsychotic drugs, use ARISTADA cautiously in patients with a history of seizures or with conditions that lower the seizure threshold. Conditions that lower the seizure threshold may be more prevalent in a population of 65 years or older.

5.12 Potential for Cognitive and Motor Impairment

ARISTADA, like other antipsychotics, has the potential to impair judgment, thinking or motor skills. Patients should be cautioned about operating hazardous machinery, including automobiles, until they are reasonably certain that therapy with ARISTADA does not affect them adversely.

5.13 Body Temperature Regulation

Disruption of the body's ability to reduce core body temperature has been attributed to antipsychotic agents. Appropriate care is advised when prescribing ARISTADA for patients who will be experiencing conditions which may contribute to an elevation in core body temperature, (e.g., exercising strenuously, exposure to extreme heat, receiving concomitant medication with anticholinergic activity, or being subject to dehydration).

5.14 Dysphagia

Esophageal dysmotility and aspiration have been associated with antipsychotic drug use. ARISTADA and other antipsychotic drugs should be used cautiously in patients at risk for aspiration pneumonia.

6 ADVERSE REACTIONS

The following are discussed in more details in other sections of the labeling:

- Increased Mortality in Elderly Patients with Dementia-related Psychosis [see Boxed Warning, Warnings and Precautions (5.1)]
- Cerebrovascular Adverse Reactions, Including Stroke [see Boxed Warning, Warnings and Precautions (5.2)]
- Neuroleptic Malignant Syndrome [see Warnings and Precautions (5.4)]
- Tardive Dyskinesia [see Warnings and Precautions (5.5)]
- Metabolic Changes [see Warnings and Precautions (5.6)]
- Pathological Gambling and Other Compulsive Behaviors [see Warnings and Precautions (5.7)]
- Orthostatic Hypotension [see Warnings and Precautions (5.8)]
- Falls [see Warnings and Precautions (5.9)]
- Leukopenia, Neutropenia, and Agranulocytosis [see Warnings and Precautions (5.10)]
- Seizures [see Warnings and Precautions (5.11)]
- Potential for Cognitive and Motor Impairment [see Warnings and Precautions (5.12)]
- Body Temperature Regulation [see Warnings and Precautions (5.13)]
- Dysphagia [see Warnings and Precautions (5.14)]

6.1 Clinical Studies Experience

Because clinical trials are conducted under widely varying conditions, adverse reaction rates observed in the clinical trials of a drug cannot be directly compared to rates in the clinical trials of another drug and may not reflect the rates observed in practice.

ARISTADA

Patient Exposure

ARISTADA has been evaluated for safety in 1180 adult patients in clinical trials in schizophrenia.

Commonly Observed Adverse Reactions

The most common adverse reaction (incidence ≥5% and at least twice the rate of placebo in patients treated with ARISTADA) was akathisia.

Adverse Reactions Occurring at an Incidence of 2% or More in ARISTADA-Treated Patients

Adverse reactions associated with the use of ARISTADA (incidence of 2% or greater, rounded to the nearest percent and ARISTADA incidence greater than placebo) that occurred are shown in Table 8.

Table 8: Adverse Reaction in 2% or More of ARISTADA-Treated Patients and That Occurred at Greater Incidence than in the Placebo-Treated Patients in the 12-Week, Placebo-Controlled, Fixed-Dose Schizophrenia Trial
Adverse Reaction System Organ Class Preferred Term | Placebo N=207 (%) | Aripiprazole Lauroxil
Adverse Reaction System Organ Class Preferred Term | Placebo N=207 (%) | 441 mg N=207 (%) | 882 mg N=208 (%)
General disorders and administration site conditions
Injection site pain | 2 | 3 | 4
Investigations
Increased weight | 1 | 2 | 2
Increased blood creatine phosphokinase | 0 | 2 | 1
Nervous system disorders
Akathisia | 4 | 11 | 11
Headache | 3 | 3 | 5
Psychiatric disorders
Insomnia | 2 | 3 | 4
Restlessness | 1 | 3 | 1

In an open label pharmacokinetic study, the adverse reactions associated with the use of 441 mg monthly, 882 mg every 6 weeks, and 1064 mg every 2 months were similar across the dose groups.

Injection Site Reactions

Injection site reactions were reported by 4% of patients treated with 441 mg ARISTADA and 5% of patients treated with 882 mg ARISTADA compared to 2% of patients treated with placebo. Most of these were injection site pain (3%, 4% and 2% in the 441 mg ARISTADA, 882 mg ARISTADA and placebo groups, respectively) and most were associated with the first injection, and decreased with each subsequent injection to less than or equal to 1% for both doses of ARISTADA and placebo. Other injection site reactions (induration, swelling and redness) occurred at less than 1%. In an open label pharmacokinetic study evaluating 441 mg monthly, 882 mg every 6 weeks, and 1064 mg every 2 months, injection site reactions were similar across the dose groups.

Extrapyramidal Symptoms

In the 12-week schizophrenia efficacy study [see Clinical Studies (14)], for ARISTADA-treated patients, the incidence of other EPS-related events, excluding akathisia and restlessness, was 5% and 7% for patients on 441 mg and 882 mg, respectively, versus 4% for placebo-treated patient (Table 9).

Table 9: Incidence of EPS Compared to Placebo
 |  | ARISTADA
Adverse Reaction Term | Placebo N=207 (%) | 441 mg N=207 (%) | 882 mg N=208 (%)
Akathisia | 4 | 11 | 11
Restlessness | 1 | 3 | 1
Other EPS | 4 | 5 | 7
Dystonia | 1 | 2 | 2
Parkinsonism | 3 | 3 | 4

Dystonia

Symptoms of dystonia, prolonged abnormal contractions of muscle groups, may occur in susceptible individuals during the first few days of treatment. Dystonic symptoms include: spasm of the neck muscles, sometimes progressing to tightness of the throat, swallowing difficulty, difficulty breathing, and/or protrusion of the tongue. While these symptoms can occur at low doses, they occur more frequently and with greater severity with high potency and at higher doses of first generation antipsychotic drugs. An elevated risk of acute dystonia is observed in males and younger age groups.

Other Adverse Reactions Observed in Clinical Studies

The following listing does not include reactions: 1) already listed in previous tables or elsewhere in labeling, 2) for which a drug cause was remote, 3) which were so general as to be uninformative, 4) which were not considered to have significant clinical implications, or 5) which occurred at a rate equal to or less than placebo.

Cardiac – angina pectoris, tachycardia, palpitations

Gastrointestinal disorders – constipation, dry mouth

General disorders – asthenia

Musculoskeletal – muscular weakness

Nervous system disorders – dizziness

Psychiatric disorders – anxiety, suicide

Adverse Reactions Reported in Clinical Trials with Oral Aripiprazole

The following is a list of additional adverse reactions that have been reported in clinical trials with oral aripiprazole and not reported above for ARISTADA.

Blood and Lymphatic System Disorders: thrombocytopenia

Cardiac Disorders: bradycardia, atrial flutter, cardiorespiratory arrest, atrioventricular block, atrial fibrillation, myocardial ischemia, myocardial infarction, cardiopulmonary failure

Eye Disorders: photophobia, diplopia

Gastrointestinal Disorders: gastroesophageal reflux disease

General Disorders and Administration Site Conditions: peripheral edema, chest pain, face edema

Hepatobiliary Disorders: hepatitis, jaundice

Immune System Disorders: hypersensitivity

Injury, Poisoning, and Procedural Complications: fall, heat stroke

Investigations: blood prolactin decreased, weight decreased, hepatic enzyme increased, blood glucose increased, blood lactate dehydrogenase increased, gamma glutamyl transferase increased, blood prolactin increased, blood urea increased, blood creatinine increased, blood bilirubin increased, electrocardiogram QT prolonged, glycosylated hemoglobin increased

Metabolism and Nutrition Disorders: anorexia, hypokalemia, hyponatremia, hypoglycemia

Musculoskeletal and Connective Tissue Disorders: muscle tightness, rhabdomyolysis, mobility decreased

Nervous System Disorders: memory impairment, cogwheel rigidity, hypokinesia, myoclonus, bradykinesia, akinesia, coordination abnormal, speech disorder, choreoathetosis

Psychiatric Disorders: aggression, loss of libido, delirium, libido increased, anorgasmia, tic, homicidal ideation, catatonia, sleep walking

Renal and Urinary Disorders: urinary retention, nocturia

Reproductive System and Breast Disorders: erectile dysfunction, gynaecomastia, menstruation irregular, amenorrhea, breast pain, priapism

Respiratory, Thoracic, and Mediastinal Disorders: nasal congestion, dyspnea

Skin and Subcutaneous Tissue Disorders: rash, hyperhidrosis, pruritus, photosensitivity reaction, alopecia, urticaria

Vascular Disorders: hypotension, hypertension

6.2 Postmarketing Experience

The following adverse reactions have been identified during post-approval use of oral aripiprazole. Because these reactions are reported voluntarily from a population of uncertain size, it is not always possible to reliably estimate their frequency or to establish a causal relationship to drug exposure: occurrences of allergic reaction (anaphylactic reaction, angioedema, laryngospasm, pruritus/urticaria, or oropharyngeal spasm), pathological gambling, hiccups, blood glucose fluctuation, oculogyric crisis, drug reaction with eosinophilia and systemic symptoms (DRESS), and fecal incontinence.

7 DRUG INTERACTIONS

7.1 Drugs Having Clinically Important Interactions with ARISTADA

Table 10: Clinically Important Drug Interactions with ARISTADA
Strong CYP3A4 Inhibitors and CYP2D6 Inhibitors
Clinical Impact: | The concomitant use of oral aripiprazole with strong CYP3A4 or CYP2D6 inhibitors increased the exposure of aripiprazole compared to the use of oral aripiprazole alone [see Clinical Pharmacology (12.3)].
Intervention: | With concomitant use of ARISTADA with a strong CYP3A4 inhibitor or CYP2D6 inhibitor for more than 2 weeks, reduce the ARISTADA dose [see Dosage and Administration (2.4)].
Examples: | itraconazole, clarithromycin, quinidine, fluoxetine, paroxetine
Strong CYP3A4 Inducers
Clinical Impact: | The concomitant use of oral aripiprazole and carbamazepine decreased the exposure of aripiprazole compared to the use of oral aripiprazole alone [see Clinical Pharmacology (12.3)].
Intervention: | With concomitant use of ARISTADA with a strong CYP3A4 inducer for more than 2 weeks consider increasing the ARISTADA dose [see Dosage and Administration (2.4)].
Examples: | carbamazepine, rifampin
Antihypertensive Drugs
Clinical Impact: | Due to its alpha adrenergic antagonism, aripiprazole has the potential to enhance the effect of certain antihypertensive agents.
Intervention: | Monitor blood pressure and adjust dose accordingly [see Warnings and Precautions (5.8)].
Examples: | carvedilol, lisinopril, prazosin
Benzodiazepines
Clinical Impact: | The intensity of sedation was greater with the combination of oral aripiprazole and lorazepam as compared to that observed with aripiprazole alone. The orthostatic hypotension observed was greater with the combination as compared to that observed with lorazepam alone [see Warnings and Precautions (5.8)].
Intervention: | Monitor sedation and blood pressure. Adjust dose accordingly.
Example: | lorazepam

7.2 Drugs Having No Clinically Important Interactions with ARISTADA

Based on pharmacokinetic studies with oral aripiprazole, no dosage adjustment of ARISTADA is required when administered concomitantly with famotidine, valproate, or lithium [see Clinical Pharmacology (12.3)].

In addition, no dosage adjustment is necessary for substrates of CYP2D6 (e.g., dextromethorphan, fluoxetine, paroxetine, or venlafaxine), CYP2C9 (e.g., warfarin), CYP2C19 (e.g., omeprazole, warfarin, escitalopram), or CYP3A4 (e.g., dextromethorphan) when co-administered with ARISTADA. Additionally, no dosage adjustment is necessary for valproate, lithium, lamotrigine, or sertraline when co-administered with ARISTADA [see Clinical Pharmacology (12.3)].

8 USE IN SPECIFIC POPULATIONS

8.1 Pregnancy

Pregnancy Exposure Registry

There is a pregnancy exposure registry that monitors pregnancy outcomes in women exposed to ARISTADA during pregnancy. For more information, contact the National Pregnancy Registry for Atypical Antipsychotics at 1-866-961-2388 or visit
http://womensmentalhealth.org/clinical-and-research-programs/pregnancyregistry/.

Risk Summary

Neonates exposed to antipsychotic drugs, including ARISTADA, during the third trimester of pregnancy are at risk for extrapyramidal and/or withdrawal symptoms following delivery. Limited published data on aripiprazole use in pregnant women are not sufficient to inform any drug-associated risks for birth defects or miscarriage (see Clinical Considerations). Overall available data from published epidemiologic studies of pregnant women exposed to aripiprazole have not established a drug-associated risk of major birth defects, miscarriage, or adverse maternal outcomes. There are risks to the mother associated with untreated schizophrenia and with exposure to antipsychotics, including ARISTADA, during pregnancy (see Clinical Considerations). Aripiprazole exposure during pregnancy may decrease milk supply in the post-partum period [see Use in Specific Populations (8.2)].

No teratogenicity was observed in animal reproductive studies with intramuscular administration of aripiprazole lauroxil to rats and rabbits during organogenesis at doses up to 5 and 15 times, respectively, the maximum recommended human dose (MRHD) of 1,064 mg based on body surface area (mg/m^2). However, aripiprazole caused developmental toxicity and possible teratogenic effects in rats and rabbits (see Data). The background risk of major birth defects and miscarriage for the indicated population are unknown. In the U.S. general population, the estimated background risk of major birth defects and miscarriage in clinically recognized pregnancies is 2 to 4% and 15 to 20%, respectively. Advise pregnant women of the potential risk to a fetus.

Clinical Considerations

Disease-associated maternal and/or embryo/fetal risk

There is a risk to the mother from untreated schizophrenia, including increased risk of relapse, hospitalization, and suicide. Schizophrenia is associated with increased adverse perinatal outcomes, including preterm birth. It is not known if this is a direct result of the illness or other comorbid factors.

Fetal/Neonatal Adverse Reactions

Extrapyramidal and/or withdrawal symptoms, including agitation, hypertonia, hypotonia, tremor, somnolence, respiratory distress and feeding disorder have been reported in neonates who were exposed to antipsychotic drugs during the third trimester of pregnancy. These symptoms have varied in severity. Monitor neonates for extrapyramidal and/or withdrawal symptoms and manage symptoms appropriately. Some neonates recover within hours or days without specific treatment; others required prolonged hospitalization.

Data

Animal Data for Aripiprazole Lauroxil

Aripiprazole lauroxil did not cause adverse developmental or maternal effects in rats or rabbits when administered intramuscularly during the period of organogenesis at doses of 18, 49, or 144 mg/animal in pregnant rats which are approximately 0.6 to 5 times the MRHD of 1064 mg on mg/m^2 basis, and at doses of 241, 723, and 2893 mg/animal in pregnant rabbits which are approximately 1 to 15 times the MRHD on mg/m^2 basis. However, aripiprazole caused developmental toxicity and possible teratogenic effects in rats and rabbits [see Data below].

Animal Data for Aripiprazole

Pregnant rats were treated with oral doses of 3, 10, and 30 mg/kg/day which are approximately 1 to 10 times the oral MRHD of 30 mg/day on mg/m^2 basis of aripiprazole during the period of organogenesis. Treatment at the highest dose caused a slight prolongation of gestation and delay in fetal development, as evidenced by decreased fetal weight, and undescended testes. Delayed skeletal ossification was observed at 3 and 10 times the oral MRHD on mg/m^2 basis.

At 3 and 10 times the oral MRHD on mg/m^2 basis, delivered offspring had decreased body weights. Increased incidences of hepatodiaphragmatic nodules and diaphragmatic hernia were observed in offspring from the highest dose group (the other dose groups were not examined for these findings). A low incidence of diaphragmatic hernia was also seen in the fetuses exposed to the highest dose. Postnatally, delayed vaginal opening was seen at 3 and 10 times the oral MRHD on mg/m^2 basis and impaired reproductive performance (decreased fertility rate, corpora lutea, implants, live fetuses, and increased post-implantation loss, likely mediated through effects on female offspring) along with some maternal toxicity were seen at the highest dose; however, there was no evidence to suggest that these developmental effects were secondary to maternal toxicity.

In pregnant rabbits treated with oral doses of 10, 30, and 100 mg/kg/day which are 2 to 11 times human exposure at the oral MRHD based on AUC and 6 to 65 times the oral MRHD on mg/m^2 basis of aripiprazole during the period of organogenesis decreased maternal food consumption and increased abortions were seen at the highest dose as well as increased fetal mortality. Decreased fetal weight and increased incidence of fused sternebrae were observed at 3 and 11 times the oral MRHD based on AUC.

In rats treated with oral doses of 3, 10, and 30 mg/kg/day which are 1 to 10 times the oral MRHD on mg/m^2 basis of aripiprazole perinatally and postnatally (from day 17 of gestation through day 21 postpartum), slight maternal toxicity and slightly prolonged gestation were seen at the highest dose. An increase in stillbirths and decreases in pup weight (persisting into adulthood) and survival were also seen at this dose.

8.2 Lactation

Risk Summary

Aripiprazole is present in human breast milk. Based on published case reports and pharmacovigilance reports, aripiprazole exposure during pregnancy and/or the postpartum period may lead to clinically relevant decreases in milk supply which may be reversible with discontinuation of the drug. There are also reports of aripiprazole exposure during pregnancy and no maternal milk supply in the post-partum period. Effects on milk supply may be mediated through decreases in prolactin levels, which have been observed [see Adverse Reactions (6.1)]. Monitor the breastfeed infant for dehydration and lack of appropriate weight gain. The development and health benefits of breastfeeding should be considered along with the mother's clinical need for ARISTADA and any potential adverse effects on the breastfed infant from ARISTADA or from the underlying maternal condition.

8.4 Pediatric Use

Safety and effectiveness of ARISTADA in patients <18 years of age have not been evaluated.

8.5 Geriatric Use

Safety and effectiveness of ARISTADA in patients >65 years of age have not been evaluated.

Elderly patients with dementia-related psychosis treated with antipsychotic drugs are at an increased risk of death. ARISTADA is not approved for the treatment of patients with dementia-related psychosis [see Warnings and Precautions (5.1, 5.2)].

8.6 CYP2D6 Poor Metabolizers

Dosage adjustment is recommended in known CYP2D6 poor metabolizers due to high aripiprazole concentrations. Approximately 8% of Caucasians and 3-8% of Black/African Americans cannot metabolize CYP2D6 substrates and are classified as poor metabolizers (PM) [see Dosage and Administration (2.4), Clinical Pharmacology (12.3)].

8.7 Hepatic and Renal Impairment

No dosage adjustment for ARISTADA is required based on a patient's hepatic function (mild to severe hepatic impairment, Child-Pugh score between 5 and 15), or renal function (mild to severe renal impairment, glomerular filtration rate between 15 and 90 mL/minute) [see Clinical Pharmacology (12.3)].

8.8 Other Specific Populations

No dosage adjustment for ARISTADA is required on the basis of a patient's sex, race, or smoking status [see Clinical Pharmacology (12.3)].

10 OVERDOSAGE

10.1 Human Experience

Common adverse reactions (reported in at least 5% of all overdose cases) reported with oral aripiprazole overdosage (alone or in combination with other substances) include vomiting, somnolence, and tremor. Other clinically important signs and symptoms observed in one or more patients with aripiprazole overdoses (alone or with other substances) include acidosis, aggression, aspartate aminotransferase increased, atrial fibrillation, bradycardia, coma, confusional state, convulsion, blood creatine phosphokinase increased, depressed level of consciousness, hypertension, hypokalemia, hypotension, lethargy, loss of consciousness, QRS complex prolonged, QT prolonged, pneumonia aspiration, respiratory arrest, status epilepticus, and tachycardia.

10.2 Management of Overdosage

In case of overdosage, call the Poison control center immediately at 1-800-222-1222.

11 DESCRIPTION

ARISTADA contains aripiprazole lauroxil, an atypical antipsychotic.

The chemical name of aripiprazole lauroxil is 7-{4-[4-(2,3-dichlorophenyl)-piperazin-1-yl]butoxy}-2-oxo-3,4-dihydro-2H-quinolin-1-yl)methyl dodecanoate. The empirical formula is C36H51Cl2N3O4 and its molecular weight is 660.7 g/mol. The chemical structure is:

ARISTADA is available as a white to off-white sterile aqueous extended-release injectable suspension for intramuscular injection in the following strengths of aripiprazole lauroxil (and deliverable volumes from a single-dose pre-filled syringe): 441 mg (1.6 mL), 662 mg (2.4 mL), 882 mg (3.2 mL) and 1064 mg (3.9 mL). The inactive ingredients include sorbitan monolaurate (3.8 mg/mL), polysorbate 20 (1.5 mg/mL), sodium chloride (6.1 mg/mL), sodium phosphate dibasic anhydrous (0.62 mg/mL), sodium phosphate monobasic dihydrate (0.52 mg/mL) and water for injection.

12 CLINICAL PHARMACOLOGY

12.1 Mechanism of Action

Aripiprazole lauroxil is a prodrug of aripiprazole. Following intramuscular injection, aripiprazole lauroxil is likely converted by enzyme-mediated hydrolysis to N-hydroxymethyl aripiprazole, which is then hydrolyzed to aripiprazole. The mechanism of action of aripiprazole in schizophrenia is unknown. However, efficacy could be mediated through a combination of partial agonist activity at dopamine D2 and serotonin 5-HT1A receptors and antagonist activity at 5-HT2A receptors.

12.2 Pharmacodynamics

Aripiprazole exhibits high affinity for dopamine D2 and D3 (Kis 0.34 and 0.8 nM respectively), serotonin 5-HT1A and 5-HT2A receptors (Kis 1.7 and 3.4 nM respectively), moderate affinity for dopamine D4, serotonin 5-HT2C and 5-HT7, alpha1-adrenergic and histamine H1 receptors (Kis 44 nM, 15 nM, 39 nM, 57 nM, and 61 nM, respectively), and moderate affinity for the serotonin reuptake site (Ki 98 nM). Aripiprazole has no appreciable affinity for cholinergic muscarinic receptors (IC50 > 1000 nM). Actions at receptors other than D2, 5-HT1A, and 5-HT2A could explain some of the adverse reactions of aripiprazole (e.g., the orthostatic hypotension observed with aripiprazole may be explained by its antagonist activity at adrenergic alpha1 receptors).

12.3 Pharmacokinetics

ARISTADA is a prodrug of aripiprazole and its activity is primarily due to aripiprazole, and to a lesser extent dehydro-aripiprazole (major metabolite of aripiprazole), which has been shown to have affinities for D2 receptors similar to aripiprazole and represents 30-40% of the aripiprazole exposure in plasma.

Absorption

After single intramuscular injection the appearance of aripiprazole in the systemic circulation starts from 5 to 6 days and continues to be released for an additional 36 days. Aripiprazole concentrations increase with consecutive doses of ARISTADA and reach steady-state four months following treatment initiation. The concentration-time course of dehydro-aripiprazole followed that of aripiprazole.

With the addition of a single intramuscular injection of ARISTADA INITIO and 30 mg oral aripiprazole at the time of the first ARISTADA dose, aripiprazole concentrations reach relevant levels within 4 days. Similarly, with the addition of the oral supplementation for 21 days at the time of the first ARISTADA dose, aripiprazole concentrations reach relevant levels within 4 days.

Aripiprazole exposure was similar for deltoid and gluteal intramuscular injections of 441 mg ARISTADA, thus are interchangeable.

Administration of 882 mg every 6 weeks or 1064 mg every 2 months results in plasma aripiprazole concentrations that were similar to exposure with 662 mg monthly and are within the range provided by doses of 441 mg monthly and 882 mg monthly. The doses of 441 mg monthly and 882 monthly showed a similar clinical response to each other.

Distribution

Based on population pharmacokinetic analysis, the apparent volume of distribution of aripiprazole following intramuscular injection of ARISTADA was 268 L, indicating extensive extravascular distribution following absorption. At therapeutic concentrations, aripiprazole and its major metabolite are greater than 99% bound to serum proteins, primarily to albumin. In healthy human volunteers administered 0.5 mg/day to 30 mg/day oral aripiprazole for 14 days, there was dose-dependent D2 receptor occupancy indicating brain penetration of aripiprazole in humans.

Elimination

Metabolism

The biotransformation of ARISTADA likely involves enzyme-mediated hydrolysis to form N-hydroxymethyl-aripiprazole, which subsequently undergoes hydrolysis to aripiprazole. Elimination of aripiprazole is mainly through hepatic metabolism involving CYP3A4 and CYP2D6. [see Dosage and Administration (2.4)].

Excretion

The mean aripiprazole terminal elimination half-life ranged from 53.9 days to 57.2 days after monthly, every 6-week and every 2 month injections of ARISTADA. The significantly longer aripiprazole apparent half-life compared to oral aripiprazole (mean 75 hours) is attributed to the dissolution and formation rate-limited elimination of aripiprazole following ARISTADA administration.

Drug Interaction Studies

No specific drug interaction studies have been performed with ARISTADA. The drug interaction data provided below is obtained from studies with oral aripiprazole.

Effects of other drugs on the exposures of aripiprazole and dehydro-aripiprazole are summarized in Figure 1 and Figure 2, respectively. Based on simulation, a 4.5-fold increase in mean Cmax and AUC values at steady-state is expected when extensive metabolizers of CYP2D6 are administered with both strong CYP2D6 and CYP3A4 inhibitors. After oral administration, a 3-fold increase in mean Cmax and AUC values at steady-state is expected in poor metabolizers of CYP2D6 administered with strong CYP3A4 inhibitors.

Figure 1: The Effects of Other Drugs on Aripiprazole Pharmacokinetics

Figure 2: The Effects of Other Drugs on Dehydro-aripiprazole Pharmacokinetics

The effects of aripiprazole on the exposures of other drugs are summarized in Figure 3.

Figure 3: The Effects of Oral Aripiprazole on Pharmacokinetics of Other Drugs

Specific Population Studies

A population pharmacokinetic analysis showed no effect of sex, race or smoking on ARISTADA pharmacokinetics [see Use in Specific Populations (8.8)].

Exposures of aripiprazole and dehydro-aripiprazole using oral aripiprazole in specific populations are summarized in Figure 4 and Figure 5, respectively.

Figure 4: Effects of Intrinsic Factors on Aripiprazole Pharmacokinetics

Figure 5: Effects of Intrinsic Factors on Dehydro-aripiprazole Pharmacokinetics

13 NONCLINICAL TOXICOLOGY

13.1 Carcinogenesis, Mutagenesis, Impairment of Fertility

Carcinogenesis

Lifetime carcinogenicity studies have not been conducted with aripiprazole lauroxil.

Lifetime carcinogenicity studies with oral aripiprazole have been conducted in ICR mice and in Sprague-Dawley (SD) and F344 rats. Aripiprazole was administered for 2 years in the diet at doses of 1, 3, 10, and 30 mg/kg/day to ICR mice and 1, 3, and 10 mg/kg/day to F344 rats (0.2 to 5 times and 0.3 to 3 times the oral MRHD of 30 mg/day based on mg/m^2, respectively). In addition, SD rats were dosed orally for 2 years at 10, 20, 40, and 60 mg/kg/day (3 to 19 times the oral MRHD based on mg/m^2). Aripiprazole did not induce tumors in male mice or rats. In female mice, the incidences of pituitary gland adenomas and mammary gland adenocarcinomas and adenoacanthomas were increased at dietary doses which are 0.1 to 0.9 times human exposure at the oral MRHD based on AUC and 0.5 to 5 times the oral MRHD on mg/m^2 basis. In female rats, the incidence of mammary gland fibroadenomas was increased at a dietary dose which is 0.1 times human exposure at the oral MRHD based on AUC and 3 times the oral MRHD on mg/m^2 basis; and the incidences of adrenocortical carcinomas and combined adrenocortical adenomas/carcinomas were increased at an oral dose which is 14 times human exposure at oral MRHD based on AUC and 19 times the oral MRHD on mg/m^2 basis.

Proliferative changes in the pituitary and mammary gland of rodents have been observed following chronic administration of other antipsychotic agents and are considered prolactin-mediated. The relevance for human risk of the findings of prolactin-mediated endocrine tumors in rodents is unknown.

Mutagenesis

Aripiprazole lauroxil was not mutagenic in the in vitro bacterial reverse mutation assay or clastogenic in the in vitro chromosome aberration assay in human peripheral blood lymphocytes.

Aripiprazole and its metabolite (2,3-DCPP) were clastogenic in the in vitro chromosome aberration assay in Chinese hamster lung (CHL) cells both in the presence and absence of metabolic activation. The metabolite, 2,3-DCPP, produced increases in numerical aberrations in the in vitro assay in CHL cells in the absence of metabolic activation. A positive response was obtained in the oral in vivo micronucleus assay in mice; however, the response was due to a mechanism not considered relevant to humans.

Impairment of Fertility

Animal Data for Aripiprazole Lauroxil

In a rat fertility study, aripiprazole lauroxil was administered intramuscularly. Males were treated with doses of 18, 49, or 144 mg /animal, which are approximately 0.4 to 3 times the MRHD of 1064 mg on mg/m^2 basis, on Days 1, 21, and 42 prior to and through mating; females were treated at these doses, which are approximately 0.6 to 5 times the MRHD on mg/m^2 basis, once 14 days prior to mating.

In females, persistent diestrus was observed at all doses and the mean number of cycles was significantly decreased at the highest dose together with an increase in the copulatory interval (delay in mating). Additional changes at the high dose included slight increases in corpora lutea and pre-implantation loss, decline in mating, fertility, and fecundity indices in females and lower mating and fertility indices in males.

Animal Data for Aripiprazole

Female rats were treated with oral aripiprazole doses of 2, 6, and 20 mg/kg/day, which are 0.6 to 6 times the oral MRHD of 30 mg/day on mg/m^2 basis, from 2 weeks prior to mating through day 7 of gestation. Estrous cycle irregularities and increased corpora lutea were seen at all doses, but no impairment of fertility was observed. Increased pre-implantation loss was found at 2 and 6 times the oral MRHD on mg/m^2 basis and decreased fetal weight was noted at the highest dose which is 6 times the oral MRHD on mg/m^2 basis.

Male rats were treated with oral aripiprazole doses of 20, 40, and 60 mg/kg/day, which are 6 to 19 times the oral MRHD on mg/m^2 basis, from 9 weeks prior to and through mating. Disturbances in spermatogenesis at the highest dose and prostate atrophy at the mid and high doses were noted which are 13 and 19 times the oral MRHD on mg/m^2 basis, but no impairment of fertility was observed.

13.2 Animal Toxicology and/or Pharmacology

Intramuscular administration of aripiprazole lauroxil to rats and dogs was associated with injection site tissue reactions at all doses in rats treated up to 6 months at doses of 15, 29, and 103 mg/animal (which are approximately 0.3 to 2 times and 0.5 to 3 times the MRHD of 1064 mg on mg/m^2 basis in males and females, respectively) and in dogs treated up to 9 months at doses of 147, 662, and 2058 mg/animal (which are approximately 0.5 to 6 times and 0.6 to 8 times the MRHD in males and females, respectively on mg/m^2 basis). These injection site tissue reactions consisted of localized granulomatous inflammation and granuloma formation. Transiently impaired limb function and swelling occurred in dogs. The granulomas did not completely resolve 2 months following the last injection in the 6 month rat study and 4 months following the last injection in the 9 month dog study (the low dose groups were not examined for reversibility in these studies).

Orally administered aripiprazole produced retinal degeneration in albino rats in a 26-week chronic toxicity study at a dose of 60 mg/kg, which is 19 times the oral MRHD of 30 mg/day on mg/m^2 basis, and in a 2-year carcinogenicity study at doses of 40 mg/kg and 60 mg/kg, which are 13 and 19 times the oral MRHD on mg/m^2 basis and 7 to 14 times human exposure at the oral MRHD based on AUC. Evaluation of the retinas of albino mice and of monkeys did not reveal evidence of retinal degeneration. Additional studies to further evaluate the mechanism have not been performed. The relevance of this finding to human risk is unknown.

14 CLINICAL STUDIES

Efficacy of ARISTADA (441 mg monthly and 882 mg monthly)

The efficacy of ARISTADA in the treatment of patients with schizophrenia was established, in part, on the basis of efficacy data from trials with the oral formulation of aripiprazole. In addition, the efficacy of ARISTADA was established in a 12-week, randomized, double-blind, placebo-controlled, fixed-dose study in adult patients with schizophrenia meeting DSM-IV TR criteria [Study 1, n = 622; 207 (ARISTADA 441 mg monthly), 208 (ARISTADA 882 mg monthly), and 207 (placebo)]. After establishing tolerability to oral aripiprazole, patients received oral aripiprazole or placebo daily for the first 3 weeks. The intramuscular (IM) injections were administered on Days 1, 29 and 57.

Efficacy was assessed using Positive and Negative Syndrome Scale (PANSS) and Clinical Global Impression Improvement Scale (CGI-I):

- The PANSS is a 30-item scale that measures positive symptoms of schizophrenia (7 items), negative symptoms of schizophrenia (7 items), and general psychopathology (16 items), each rated on a scale of 1 (absent) to 7 (extreme). Total PANSS scores range from 30 to 210.
- The CGI-I rates improvement in mental illness on a scale of 1 (very much improved) to 7 (very much worse) based on the change from baseline in clinical condition.

Eligible patients were 18 to 70 years of age with PANSS total score of 70 to 120 and a score of ≥4 for at least 2 of the selected Positive Scale items. Patients were also required to have a CGI-S score of ≥4.

The primary efficacy variable was the change from baseline to endpoint (Day 85) in PANSS total score. Statistically significant separation from placebo on PANSS total score change was observed in each ARISTADA dose group (Table 11).

Table 11: Primary Efficacy Results
Study Number | Treatment Group | Primary Efficacy Measure: PANSS Total Score
Study Number | Treatment Group | Mean Baseline Score (SD) | LS Mean Change from Baseline (SE) | Placebo-subtracted Differencea (95% CI)
Study 1 | ARISTADA 441 mg monthlyb | 92.6 (10.2) | -20.9 (1.4) | -10.9 (-14.5, -7.3)
 | ARISTADA 882 mg monthlyb | 92.0 (10.8) | -21.8 (1.4) | -11.9 (-15.4, -8.3)
 | Placebo | 93.9 (11.3) | -9.8 (1.4) | --
SD: standard deviation; SE: standard error; LS Mean: least-squares mean; CI: confidence interval, not adjusted for multiple comparisons.
a Difference (drug minus placebo) in least-squares mean change from baseline.
b Doses that are demonstrated to be effective.

The visit-wise mean change from baseline on PANSS total score change for each treatment group is shown in Figure 6.

Figure 6: Change from Baseline in PANSS Total Score

Abbreviations: AL= ARISTADA; PBO=placebo; PANSS=Positive and Negative Syndrome Scale.

Vertical dotted line indicates end of oral supplementation.

Subgroup analyses did not suggest any clear evidence of differential responsiveness in treatment outcome as a function of age, gender, race, or weight.

The secondary efficacy endpoint was defined as the CGI-I score at Day 85. Both ARISTADA treatment groups demonstrated statistically significantly better CGI-I scores versus placebo.

Efficacy of ARISTADA 662 mg Monthly, 882 mg Every 6 Weeks and 1064 mg Every 2 Months

The efficacy of ARISTADA 662 mg monthly, 882 mg every 6 weeks, and 1064 mg every 2 months in the treatment of adults with schizophrenia was established by pharmacokinetic bridging which demonstrated that these dosing regimens resulted in plasma aripiprazole concentrations that are within the range provided by doses of 441 mg monthly and 882 mg monthly. As depicted in Figure 6, the doses of 441 mg monthly and 882 mg monthly showed clinical responses similar to each other in the ARISTADA placebo-controlled trial.

16 HOW SUPPLIED/ STORAGE AND HANDLING

16.1 How Supplied

ARISTADA extended-release injectable suspension is available in strengths of 441 mg in 1.6 mL, 662 mg in 2.4 mL, 882 mg in 3.2 mL and 1064 mg in 3.9 mL. The kit contains a 5-mL pre-filled syringe containing ARISTADA as a sterile white to off-white aqueous extended-release injectable suspension with safety needles.

- The 441 mg strength kit (NDC 65757-401-03; light blue label) contains three safety needles; a 1-inch (25 mm) 21 gauge, a 1½-inch (38 mm) 20 gauge, and a 2-inch (50 mm) 20 gauge needle.
- The 662 mg strength kit (NDC 65757-402-03; green label) contains two safety needles; a 1½-inch (38 mm) 20 gauge and a 2-inch (50 mm) 20 gauge needle.
- The 882 mg strength kit (NDC 65757-403-03; burgundy label) contains two safety needles; a 1½-inch (38 mm) 20 gauge and a 2-inch (50 mm) 20 gauge needle.
- The 1064 mg strength kit (NDC 65757-404-03; dark blue label) contains two safety needles; a 1½-inch (38 mm) 20 gauge and a 2-inch (50 mm) 20 gauge needle.

16.2 Storage

Store at room temperature 20°C to 25°C (68°F to 77°F) with excursions permitted between 15°C and 30°C (between 59°F and 86°F).

17 PATIENT COUNSELING INFORMATION

Advise patients to read FDA-approved patient labeling (Medication Guide).

Pathological Gambling and Other Compulsive Behaviors

Advise patients and their caregivers of the possibility that they may experience compulsive urges to shop, intense urges to gamble, compulsive sexual urges, binge eating and/or other compulsive urges and the inability to control these urges. In some cases, but not all, the urges were reported to have stopped when the dose was reduced or stopped [see Warnings and Precautions (5.7)].

Neuroleptic Malignant Syndrome

Counsel patients about a potentially fatal adverse reaction referred to as NMS that has been reported in association with administration of antipsychotic drugs. Advise patients to contact a healthcare provider or report to the emergency room if they experience signs or symptoms of NMS [see Warnings and Precautions (5.4)].

Tardive Dyskinesia

Advise patients that abnormal involuntary movements have been associated with administration of antipsychotic drugs. Counsel patients to notify their healthcare provider if they notice any movements which they cannot control in their face, tongue, or other body part [see Warnings and Precautions (5.5)].

Metabolic Changes (Hyperglycemia and Diabetes Mellitus, Dyslipidemia, and Weight Gain)

Educate patients about the risk of metabolic changes, how to recognize symptoms of hyperglycemia and diabetes mellitus, and the need for specific monitoring, including blood glucose, lipids, and weight [see Warnings and Precautions (5.6)].

Orthostatic Hypotension

Educate patients about the risk of orthostatic hypotension (symptoms include feeling dizzy or lightheaded upon standing), particularly at the time of initiating treatment, re-initiating treatment, or increasing the dose [see Warnings and Precautions (5.8)].

Falls

Advise patients and their caregivers of the possibility that they may experience somnolence, postural hypotension, or motor and sensory instability, which may lead to the risk of falls, particularly in patients with diseases, conditions, or medications that could exacerbate these effects [see Warnings and Precautions (5.9)].

Leukopenia/ Neutropenia

Advise patients with a pre-existing low WBC count or a history of drug-induced leucopenia/neutropenia that they should have their CBC monitored while receiving ARISTADA [see Warnings and Precautions (5.10)].

Interference with Cognitive and Motor Performance

Because ARISTADA may have the potential to impair judgment, thinking or motor skills, instruct patients to be cautious about operating hazardous machinery, including automobiles, until they are reasonably certain that ARISTADA therapy does not affect them adversely [see Warnings and Precautions (5.12)].

Heat Exposure and Dehydration

Advise patients regarding appropriate care in avoiding overheating and dehydration [see Warnings and Precautions (5.13)].

Concomitant Medication

Advise patients to inform their physicians if they are taking, or plan to take, any prescription or over-the-counter drugs, since there is a potential for interactions [see Drug Interactions (7)].

Pregnancy

Advise patients to notify their healthcare provider if they become pregnant or intend to become pregnant during treatment with ARISTADA. Advise patients that ARISTADA may cause extrapyramidal and/or withdrawal symptoms (agitation, hypertonia, hypotonia, tremor, somnolence, respiratory distress, and feeding disorder) in a neonate. Advise patients that there is a pregnancy registry that monitors pregnancy outcomes in women exposed to ARISTADA during pregnancy [see Use in Specific Populations (8.1)].

Lactation

ARISTADA use during pregnancy may affect milk supply. Advise the lactating patient to discuss any plans for breastfeeding with their healthcare provider, and to monitor the breastfed infant for dehydration and lack of appropriate weight gain [see Use in Specific Populations (8.2)].

For additional information, visit www.ARISTADA.com or call 1-866-274-7823

Manufactured and marketed by:

Alkermes, Inc.

Waltham, MA 02451

Alkermes

©2025 Alkermes, Inc. All rights reserved.

ALKERMES® is a registered trademark of Alkermes, Inc., ARISTADA® is a registered trademark used by Alkermes, Inc. under license and ARISTADA INITIO® is a registered trademark used by Alkermes, Inc. under license.

Printed in U.S.A.

MEDICATION GUIDE
ARISTADA® (air-is-TAH-dah)
(aripiprazole lauroxil)
extended-release injectable suspension, for intramuscular use

What is the most important information I should know about ARISTADA?
Each injection of ARISTADA must be administered by a healthcare professional only.
ARISTADA may cause serious side effects, including:

- Increased risk of death in elderly people with dementia-related psychosis. ARISTADA increases the risk of death in elderly people who have lost touch with reality (psychosis) due to confusion and memory loss (dementia). ARISTADA is not for the treatment of people with dementia-related psychosis.

What is ARISTADA?
ARISTADA is a prescription medicine used to treat schizophrenia in adults.
It is not known if ARISTADA is safe and effective in children under 18 years of age.

Do not receive ARISTADA if you are allergic to aripiprazole or any of the ingredients in ARISTADA. See the end of this Medication Guide for a complete list of ingredients in ARISTADA.

Before receiving ARISTADA, tell your healthcare provider about all of your medical conditions, including if you:

- have never taken ABILIFY®, ABILIFY MAINTENA® or any aripiprazole product before
- have or had heart problems or a stroke
- have diabetes or high blood sugar or a family history of diabetes or high blood sugar. Your healthcare provider should check your blood sugar before you start receiving ARISTADA and during your treatment.
- have or had low or high blood pressure
- have or had seizures (convulsions)
- have or had a low white blood cell count
- have problems that may affect you receiving an injection in your buttocks or your arm
- are pregnant or plan to become pregnant. It is not known if ARISTADA will harm your unborn baby.
  - If you become pregnant while receiving ARISTADA, talk to your healthcare provider about registering with the National Pregnancy Registry for Atypical Antipsychotics. You can register by calling 1-866-961-2388 or visit http://womensmentalhealth.org/clinical-and-research-programs/pregnancyregistry/
- are breastfeeding or plan to breastfeed. ARISTADA can pass into your breast milk and it is not known if it may harm your baby. Talk to your healthcare provider about the best way to feed your baby if you receive ARISTADA.

Tell your healthcare provider about all the medicines you take, including prescription and over-the-counter medicines, vitamins, and herbal supplements.
ARISTADA and other medicines may affect each other causing possible serious side effects. ARISTADA may affect the way other medicines work, and other medicines may affect how ARISTADA works.
Your healthcare provider can tell you if it is safe to receive ARISTADA with your other medicines. Do not start or stop any medicines while receiving ARISTADA without talking to your healthcare provider first.

How should I receive ARISTADA?

- Follow your ARISTADA treatment schedule exactly as your healthcare provider tells you to.
- Each ARISTADA is an injection given by your healthcare provider into the muscle (intramuscular) of your arm or buttock.
- There are 2 ways to start treatment with ARISTADA:
  - Option 1: You will receive 1 dose of ARISTADA INITIO in combination with a single dose of oral aripiprazole. You may also receive your first injection of ARISTADA on the same day you receive ARISTADA INITIO or up to 10 days after you receive ARISTADA INITIO.
  - Option 2: After your first injection of ARISTADA, you will take oral aripiprazole for 21 days in a row (consecutive).
- You should not miss a dose of ARISTADA. If you miss a dose for some reason, call your healthcare provider right away to discuss what you should do next.

What should I avoid while receiving ARISTADA?

- Do not drive a car, operate hazardous machinery, or do other dangerous activities until you know how ARISTADA affects you. ARISTADA may affect your judgment, thinking or motor skills.
- Avoid becoming too hot or dehydrated while you receive ARISTADA.
  - Do not exercise too much.
  - In hot weather, stay inside in a cool place if possible.
  - Stay out of the sun.
  - Do not wear too much clothing or heavy clothing.
  - Drink plenty of water.

What are the possible side effects of ARISTADA?
ARISTADA may cause serious side effects, including:

- See “What is the most important information I should know about ARISTADA?”
- Cerebrovascular problems (including stroke) in elderly people with dementia-related psychosis that can lead to death.
- Neuroleptic malignant syndrome (NMS), a serious condition that can lead to death. Call your healthcare provider or go to the nearest hospital emergency room right away if you have some or all of the following signs symptoms of NMS:
  - high fever
  - stiff muscles
  - confusion
  - sweating
  - changes in pulse, heart rate, and blood pressure

- Uncontrolled body movements (tardive dyskinesia). ARISTADA may cause movements that you cannot control in your face, tongue, or other body parts. Tardive dyskinesia may not go away, even if you stop receiving ARISTADA. Tardive dyskinesia may also start after you stop receiving ARISTADA.
- Problems with your metabolism such as:
  - high blood sugar (hyperglycemia). Increases in blood sugar can happen in some people who receive ARISTADA. Extremely high blood sugar can lead to coma or death. If you have diabetes or risk factors for diabetes (such as being overweight or a family history of diabetes), your healthcare provider should check your blood sugar before you start receiving ARISTADA and during your treatment.
    Call your healthcare provider if you have any of these symptoms of high blood sugar while receiving ARISTADA:
    - Feel very thirsty
    - Feel very hungry
    - Feel sick to your stomach
    - Need to urinate more than usual
    - Feel weak or tired
    - Feel confused, or your breath smells fruity
  - increased fat levels (cholesterol and triglycerides) in your blood.
  - weight gain. You and your healthcare provider should check your weight regularly.
- Unusual and uncontrollable (compulsive) urges. Some people taking aripiprazole products have had strong unusual urges to gamble and gambling that cannot be controlled (compulsive gambling). Other compulsive urges include increased sexual urges, shopping, and eating or binge eating. If you or your family members notice that you are having unusual urges, talk to your healthcare provider.
- Decreased blood pressure (orthostatic hypotension). You may feel lightheaded or faint when you rise too quickly from a sitting or lying position.
- Falls. ARISTADA may make you sleepy or dizzy, may cause a decrease in your blood pressure when changing position and can slow your thinking and motor skills which may lead to falls that can cause fractures or other injuries.
- Low white blood cell count
- Seizures (convulsions)
- Problems controlling your body temperature. See “What should I avoid while receiving ARISTADA?”
- Difficulty swallowing

The most common side effects of ARISTADA include restlessness or feeling like you need to move (akathisia).
These are not all the possible side effects of ARISTADA.
Call your doctor for medical advice about side effects. You may report side effects to FDA at 1-800-FDA-1088.

General information about ARISTADA
If you would like more information, talk with your healthcare provider. You can ask your pharmacist or healthcare provider for information about ARISTADA that is written for health professionals.

What are the ingredients in ARISTADA?
Active ingredient: aripiprazole lauroxil
Inactive ingredients: sorbitan monolaurate, polysorbate 20, sodium chloride, sodium phosphate dibasic anhydrous, sodium phosphate monobasic dihydrate and water for injection
Manufactured and marketed by: Alkermes, Inc., Waltham, MA 02451
For more information, go to www.ARISTADA.com or call 1-866-274-7823.

This Medication Guide has been approved by the U.S. Food and Drug Administration

Revised 12/2023

PACKAGE LABEL

Principal Display Panel - 441 mg/1.6 mL Carton Label

NDC: 65757-401-03

Rx only

Aristada®
aripiprazole lauroxil
extended-release injectable suspension

441 mg

For deltoid or gluteal intramuscular injection only

Single-dose injection - Entire Content of Syringe Must Be
Administered by Healthcare Professional Only

441 mg/1.6 mL administered monthly.

For dosing and administration instructions, please
see accompanying full prescribing information.

Dispense enclosed Medication Guide to Patient.

Store at room temperature 20°C to 25°C (68°F to 77°F)
with excursions permitted between 15°C to 30°C (59°F to 86°F)

Keep out of reach of children

PACKAGE LABEL

Principal Display Panel - 662 mg/2.4 mL Carton Label

NDC: 65757-402-03

Rx only

Aristada®
aripiprazole lauroxil
extended-release injectable suspension

662 mg

For gluteal intramuscular injection only

Single-dose injection - Entire Content of Syringe Must Be
Administered by Healthcare Professional Only

662 mg/2.4 mL administered monthly.

For dosing and administration instructions, please
see accompanying full prescribing information.

Dispense enclosed Medication Guide to Patient.

Store at room temperature 20°C to 25°C (68°F to 77°F)
with excursions permitted between 15°C to 30°C (59°F to 86°F)

Keep out of reach of children

PACKAGE LABEL

Principal Display Panel - 882 mg/3.2 mL Carton Label

NDC: 65757-403-03

Rx only

Aristada®
aripiprazole lauroxil
extended-release injectable suspension

882 mg

For gluteal intramuscular injection only

Single-dose injection - Entire Content of Syringe Must Be
Administered by Healthcare Professional Only

882 mg/3.2 mL administered monthly or every 6 weeks.

For dosing and administration instructions, please
see accompanying full prescribing information.

Dispense enclosed Medication Guide to Patient.

Store at room temperature 20°C to 25°C (68°F to 77°F)
with excursions permitted between 15°C to 30°C (59°F to 86°F)

Keep out of reach of children

PACKAGE LABEL

Principal Display Panel - 1064 mg/3.9 mL Carton Label

NDC: 65757-404-03

Rx only

Aristada®
aripiprazole lauroxil
extended-release injectable suspension

1064 mg

For gluteal intramuscular injection only

Single-dose injection - Entire Content of Syringe Must Be
Administered by Healthcare Professional Only

1064 mg/3.9 mL administered every 2 months.

For dosing and administration instructions, please
see accompanying full prescribing information.

Dispense enclosed Medication Guide to Patient.

Store at room temperature 20°C to 25°C (68°F to 77°F)
with excursions permitted between 15°C to 30°C (59°F to 86°F)

Keep out of reach of children